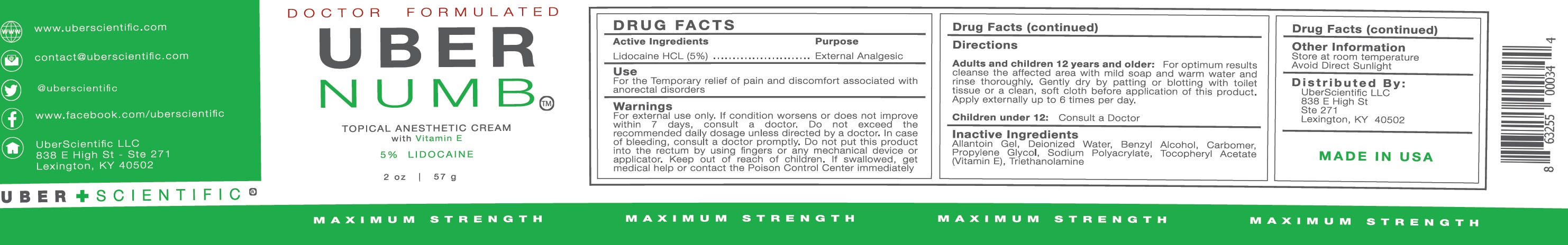 DRUG LABEL: Uber Numb
NDC: 71131-051 | Form: CREAM
Manufacturer: UBERScientific, LLC
Category: otc | Type: HUMAN OTC DRUG LABEL
Date: 20231110

ACTIVE INGREDIENTS: LIDOCAINE HYDROCHLORIDE 50 mg/1 g
INACTIVE INGREDIENTS: WATER; BENZYL ALCOHOL; CARBOXYPOLYMETHYLENE; PROPYLENE GLYCOL; .ALPHA.-TOCOPHEROL ACETATE; TROLAMINE

Uber Numb Cream

Active Ingredients

Lidocaine HCL (5%)

Purpose

External Analgesic

Uses

For the Temporary relief of pain and discomfort associated with anorectal disorders

Warnings:

For external ues only. If condition worsens or does not improve within 7 days, consult a doctor. Do not exceed the recommended daily dosage unless directed by a doctor. In case of bleeding, consult a doctor promptly. Do not put this product into the rectum by using fingers or any mechanical device or applicator.

Keep out of reach of children.

If swallowed, get medical help or contact the Poison Control Center immediately

Directions:

For optimum results cleanse the affected area with mild soap and warm water and rinse thoroughly, Gently dry by patting or blotting with toilet tissue or a clean, soft cloth before application of this product. Adults and children 12 years and older:

Apply externally up to 6 times per day.

Consult a Doctor Children under 12:

Inactive Ingredients:

Allantoin Gel, Deionized Water, Benzyl Alcohol, Carbomer, Propylene Glycol, Sodium Polyacrylate, Tocopheryl Acetate (Vitamin E), Triethanolamine

Distributed by:

UberScientific LLC 838 E High St. Ste 271

Lexington, KY 40502